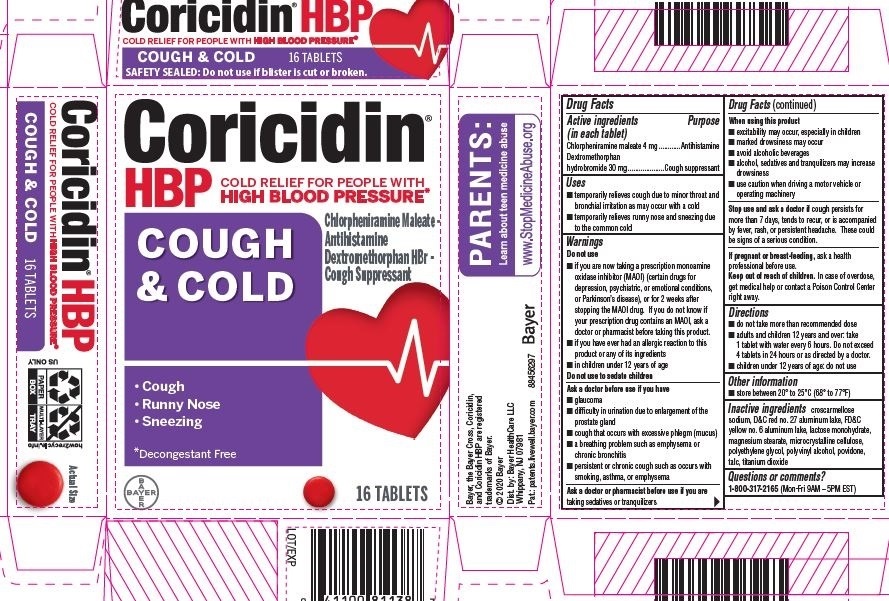 DRUG LABEL: Coricidin HBP Cough and Cold
NDC: 11523-0008 | Form: TABLET
Manufacturer: Bayer HealthCare LLC.
Category: otc | Type: HUMAN OTC DRUG LABEL
Date: 20251204

ACTIVE INGREDIENTS: DEXTROMETHORPHAN HYDROBROMIDE 30 mg/1 1; CHLORPHENIRAMINE MALEATE 4 mg/1 1
INACTIVE INGREDIENTS: ANHYDROUS LACTOSE; POLYETHYLENE GLYCOL, UNSPECIFIED; STEARIC ACID; D&C RED NO. 27 ALUMINUM LAKE; SILICON DIOXIDE; TITANIUM DIOXIDE; CROSCARMELLOSE SODIUM; POLYVINYL ALCOHOL, UNSPECIFIED; MAGNESIUM STEARATE; TALC; MICROCRYSTALLINE CELLULOSE; FD&C YELLOW NO. 6

Coricidin HBP Cough and Cold UI 1614831

Drug Facts

Active ingredients (in each tablet) Purpose

Chlorpheniramine maleate 4 mg………………………….....................Antihistamine

Dextromethorphan hydrobromide 30 mg……………………… .Cough suppressant

Uses

- temporarily relieves cough due to minor throat and bronchial irritation as may occur with a cold
- temporarily relieves runny nose and sneezing due to the common cold

Warnings

Do not use

- if you are now taking a prescription monoamine oxidase inhibitor (MAOI) (certain drugs for depression, psychiatric, or emotional conditions, or Parkinson's disease), or for 2 weeks after stopping the MAOI drug. If you do not know if your prescription drug contains an MAOI, ask a doctor or pharmacist before taking this product.
- if you have ever had an allergic reaction to this product or any of its ingredients
- in children under 12 years of age

Do not use to sedate children.

Ask a doctor before use if you have

- trouble urinating due to an enlarged prostate gland
- cough that occurs with excessive phlegm (mucus)
- a breathing problem such as emphysema or chronic bronchitis
- persistent or chronic cough such as occurs with smoking, asthma, or emphysema

Ask a doctor or pharmacist before use if you are taking sedatives or tranquilizers

When using this product

- excitability may occur, especially in children
- marked drowsiness may occur
- avoid alcoholic beverages
- alcohol, sedatives and tranquilizers may increase drowsiness
- use caution when driving a motor vehicle or operating machinery

Stop use and ask a doctor if cough persists for more than 7 days, tends to recur, or is accompanied by fever, rash, or persistent headache. These could be signs of a serious condition.

PREGNANCY OR BREAST FEEDING

If pregnant or breast-feeding, ask a health professional before use.

Keep out of reach of children. In case of overdose, get medical help or contact

a Poison Control Center right away. Abuse of this product can lead to serious injury.

Directions

- do not exceed recommended dose
- adults and children 12 years and over: take 1 tablet every 6 hours, not more

than 4 tablets in 24 hours

- children under 12 years of age: do not use

Other information

- store between 20º to 25ºC (68º to 77ºF)
- see end flap for expiration date and lot number

INACTIVE INGREDIENT

Inactive ingredients croscarmellose sodium, D&C red #27 aluminum lake, FD&C yellow #6 aluminum lake, lactose anhydrous, magnesium stearate, microcrystalline cellulose, polyethylene glycol, polyvinyl alcohol, silicon dioxide, stearic acid, talc, titanium dioxide

Questions or comments? 1-800-317-2165 (Mon-Fri 9AM - 5PM EST)

Carton 16

Coricidin®

HBP

Decongestant-Free Cold

Symptom Relief for

People with High Blood Pressure

Cold and Cough

Dextromethorphan HBr-

Cough Suppresant

Chlorpheniramine Maleate-

Antihistamine

Relieves:

- Cough
- Runny nose
- Sneezing

16 TABLETS